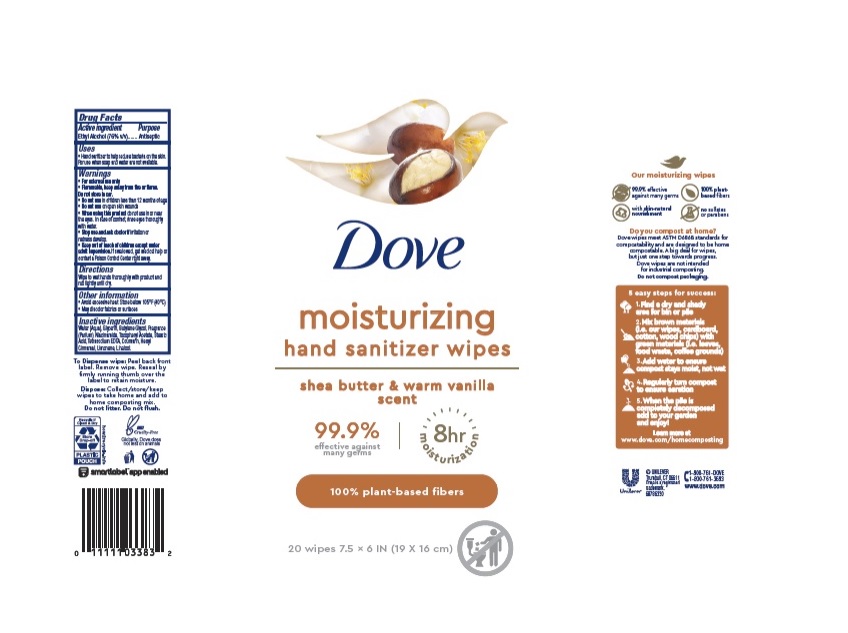 DRUG LABEL: Dove
NDC: 64942-2041 | Form: CLOTH
Manufacturer: Conopco Inc. d/b/a/ Unilever
Category: otc | Type: HUMAN OTC DRUG LABEL
Date: 20241107

ACTIVE INGREDIENTS: ALCOHOL 760 mg/1 mL
INACTIVE INGREDIENTS: STEARIC ACID; COUMARIN; .ALPHA.-TOCOPHEROL ACETATE; BUTYLENE GLYCOL; WATER; GLYCERIN; LIMONENE, (+)-; EDETATE SODIUM; .ALPHA.-HEXYLCINNAMALDEHYDE; LINALOOL, (+/-)-; NIACINAMIDE

Dove Moisturizing Hand Sanitizer Wipes Shea Butter & Warm Vanilla Scent

DOVE MOISTURIZING HAND SANITIZER WIPES SHEA BUTTER & WARM VANILLA SCENT - ethyl alcohol cloth

Dove Nourishing Hand Sanitizer Shea Butter & Warm Vanilla 8h Moisturization

Drug Facts

Active ingredient

Ethyl Alcohol 76%

Purpose

Antiseptic

Uses

• Hand sanitizer to help reduce bacteria on the skin. For use when soap and water are not available.

Warnings

For external use only
Flammable. Keep away from fire or flame

Do not store in car.
Do not use in children less than 12 months of age
Do not use on open skin wounds
When using this product, do not use in or near the eyes. In case of contact, rinse eyes thoroughly with water
Stop use and ask doctor if irritation or redness develop

• Keep out of reach of children except under adult supervision.

If swallowed, get medical help or contact a poison control Center right away.

Directions

• Wet hands thoroughly with product and rub lightly until dry.

Other information

• Avoid excessive heat. Store below 105˚F (40˚C).
• May discolor fabrics or surfaces.

Inactive ingredients

Water (Aqua), Glycerin, Butylene Glycol, Fragrance (Parfum), Niacinamide, Tocopheryl Acetate, Stearic Acid, Tetrasodium EDTA, Coumarin, Hexyl Cinnamal, Limonene, Linalool.

Questions?

1-800-761-3683